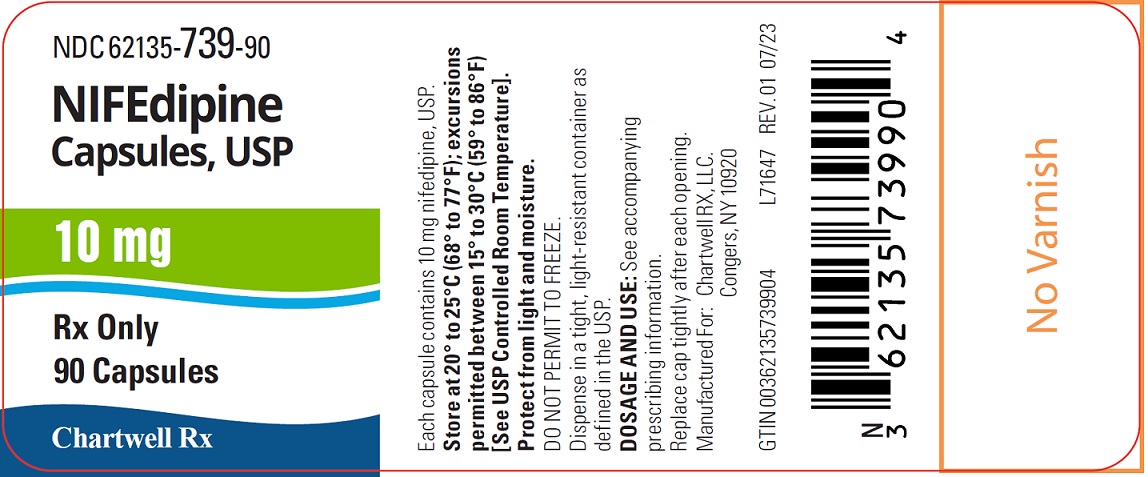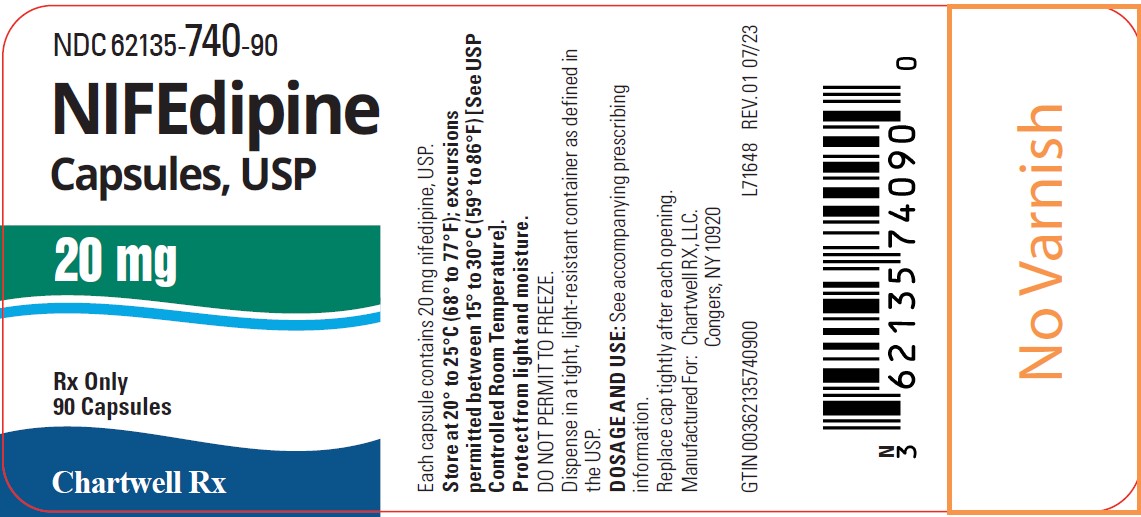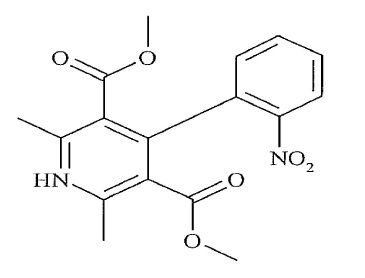 DRUG LABEL: Nifedipine
NDC: 62135-740 | Form: CAPSULE
Manufacturer: Chartwell RX, LLC
Category: prescription | Type: HUMAN PRESCRIPTION DRUG LABEL
Date: 20251217

ACTIVE INGREDIENTS: NIFEDIPINE 20 mg/1 1
INACTIVE INGREDIENTS: TITANIUM DIOXIDE; PEPPERMINT; LIGHT MINERAL OIL; WATER; FERROSOFERRIC OXIDE; FD&C RED NO. 40; FD&C YELLOW NO. 6; POLYETHYLENE GLYCOL 400; ALUMINUM OXIDE; AMMONIA; SACCHARIN SODIUM; PROPYLENE GLYCOL; METHYLPARABEN; GELATIN, UNSPECIFIED; GLYCERIN; SORBITOL; PROPYLPARABEN; SHELLAC

Nifedipine Capsule, USP
Rx only

DESCRIPTION

Nifedipine, USP is an antianginal drug belonging to a class of pharmacological agents, the calcium channel blockers. Nifedipine is 1, 4-Dihydro-2, 6-dimethyl-4-(2-nitrophenyl)-3, 5-pyridinecarboxylic acid dimethyl ester, C17H18N2O6, and has the structural formula:

Nifedipine, USP is a yellow crystalline substance, practically insoluble in water but soluble in ethanol. It has a molecular weight of 346.3. Nifedipine capsules, USP are formulated as soft gelatin capsules for oral administration, each containing 10 mg or 20 mg nifedipine, USP.

Inactive Ingredients: Nifedipine capsules, USP for oral administration contain the following inactive ingredients: glycerin, peppermint oil, polyethylene glycol and saccharin sodium. The 10 mg capsule shell contains ammonium hydroxide, gelatin, glycerin, iron oxide black, light mineral oil, methyl paraben, propylene glycol, propyl paraben, shellac glaze, sorbitol, titanium dioxide and water. The 20 mg capsule shell contains ammonium hydroxide, FD and C Red No. 40 aluminum lake, FD and C Yellow No. 6 aluminum lake, gelatin, glycerin, iron oxide black, light mineral oil, methyl paraben, propylene glycol, propyl paraben, shellac glaze, sorbitol, titanium dioxide and water.

CLINICAL PHARMACOLOGY

Nifedipine is a calcium ion influx inhibitor (slow-channel blocker or calcium ion antagonist) and inhibits the transmembrane influx of calcium ions into cardiac muscle and smooth muscle. The contractile processes of cardiac muscle and vascular smooth muscle are dependent upon the movement of extracellular calcium ions into these cells through specific ion channels. Nifedipine selectively inhibits calcium ion influx across the cell membrane of cardiac muscle and vascular smooth muscle without changing serum calcium concentrations.

Mechanism of Action

The precise means by which this inhibition relieves angina has not been fully determined, but includes at least the following two mechanisms:

1) Relaxation and Prevention of Coronary Artery Spasm

Nifedipine dilates the main coronary arteries and coronary arterioles, both in normal and ischemic regions, and is a potent inhibitor of coronary artery spasm, whether spontaneous or ergonovine-induced. This property increases myocardial oxygen delivery in patients with coronary artery spasm, and is responsible for the effectiveness of nifedipine in vasospastic (Prinzmetal's or variant) angina. Whether this effect plays any role in classical angina is not clear, but studies of exercise tolerance have not shown an increase in the maximum exercise rate-pressure product, a widely accepted measure of oxygen utilization. This suggests that, in general, relief of spasm or dilation of coronary arteries is not an important factor in classical angina.

2) Reduction of Oxygen Utilization

Nifedipine regularly reduces arterial pressure at rest and at a given level of exercise by dilating peripheral arterioles and reducing the total peripheral resistance (afterload) against which the heart works. This unloading of the heart reduces myocardial energy consumption and oxygen requirements and probably accounts for the effectiveness of nifedipine in chronic stable angina.

Pharmacokinetics and Metabolism

Nifedipine is rapidly and fully absorbed after oral administration. The drug is detectable in serum 10 minutes after oral administration, and peak blood levels occur in approximately 30 minutes. Bioavailability is proportional to dose from 10 to 30 mg; half-life does not change significantly with dose. There is little difference in relative bioavailability when nifedipine capsules are given orally and either swallowed whole, bitten and swallowed, or bitten and held sublingually. However, biting through the capsule prior to swallowing does result in slightly earlier plasma concentrations (27 ng/mL 10 minutes after 10 mg) than if capsules are swallowed intact. Nifedipine is highly bound by serum proteins. Nifedipine is extensively converted to inactive metabolites and approximately 80 percent of nifedipine and metabolites are eliminated via the kidneys. The elimination half-life of nifedipine is approximately two hours. Since hepatic biotransformation is the predominant route for the disposition of nifedipine, the pharmacokinetics may be altered in patients with chronic liver disease. Patients with hepatic impairment (liver cirrhosis) have a longer disposition half-life and higher bioavailability of nifedipine than healthy volunteers. The degree of serum protein binding of nifedipine is high (92 to 98%). Protein binding may be greatly reduced in patients with renal or hepatic impairment.

Following intravenous administration, clearance of nifedipine was decreased by 33% in elderly healthy subjects relative to young healthy subjects.

Hemodynamics

Like other slow-channel blockers, nifedipine exerts a negative inotropic effect on isolated myocardial tissue. This is rarely, if ever, seen in intact animals or man, probably because of reflex responses to its vasodilating effects. In man, nifedipine causes decreased peripheral vascular resistance and a fall in systolic and diastolic pressure, usually modest (5 to 10 mm Hg systolic), but sometimes larger. There is usually a small increase in heart rate, a reflex response to vasodilation. Measurements of cardiac function in patients with normal ventricular function have generally found a small increase in cardiac index without major effects on ejection fraction, left ventricular end diastolic pressure (LVEDP), or volume (LVEDV). In patients with impaired ventricular function, most acute studies have shown some increase in ejection fraction and reduction in left ventricular filling pressure.

Electrophysiologic Effects

Although, like other members of its class, nifedipine decreases sinoatrial node function and atrioventricular conduction in isolated myocardial preparations, such effects have not been seen in studies in intact animals or in man. In formal electrophysiologic studies, predominantly in patients with normal conduction systems, nifedipine has had no tendency to prolong atrioventricular conduction, prolong sinus node recovery time, or slow sinus rate.

INDICATIONS AND USAGE

I. Vasospastic Angina

Nifedipine is indicated for the management of vasospastic angina confirmed by any of the following criteria: 1) classical pattern of angina at rest accompanied by ST segment elevation, 2) angina or coronary artery spasm provoked by ergonovine, or 3) angiographically demonstrated coronary artery spasm. In those patients who have had angiography, the presence of significant fixed obstructive disease is not incompatible with the diagnosis of vasospastic angina, provided that the above criteria are satisfied. Nifedipine may also be used where the clinical presentation suggests a possible vasospastic component but where vasospasm has not been confirmed, e.g., where pain has a variable threshold on exertion or when angina is refractory to nitrates and/or adequate doses of beta blockers.

II. Chronic Stable Angina

(Classical Effort-Associated Angina)

Nifedipine is indicated for the management of chronic stable angina (effort-associated angina) without evidence of vasospasm in patients who remain symptomatic despite adequate doses of beta blockers and/or organic nitrates or who cannot tolerate those agents.

In chronic stable angina (effort-associated angina), nifedipine has been effective in controlled trials of up to eight weeks duration in reducing angina frequency and increasing exercise tolerance, but confirmation of sustained effectiveness and evaluation of long-term safety in these patients are incomplete.

Controlled studies in small numbers of patients suggest concomitant use of nifedipine and beta-blocking agents may be beneficial in patients with chronic stable angina, but available information is not sufficient to predict with confidence the effects of concurrent treatment, especially in patients with compromised left ventricular function or cardiac conduction abnormalities. When introducing such concomitant therapy, care must be taken to monitor blood pressure closely since severe hypotension can occur from the combined effects of the drugs. (See WARNINGS.)

CONTRAINDICATIONS

Known hypersensitivity reaction to nifedipine.

WARNINGS

Excessive Hypotension

Although, in most patients, the hypotensive effect of nifedipine is modest and well tolerated, occasional patients have had excessive and poorly tolerated hypotension. These responses have usually occurred during initial titration or at the time of subsequent upward dosage adjustment. Although patients have rarely experienced excessive hypotension on nifedipine alone, this may be more common in patients on concomitant beta blocker therapy. Although not approved for this purpose, nifedipine capsules have been used (orally and sublingually) for acute reduction of blood pressure. Several well-documented reports describe cases of profound hypotension, myocardial infarction, and death when immediate-release nifedipine was used in this way. Nifedipine capsules should not be used for the acute reduction of blood pressure.

Severe hypotension and/or increased fluid volume requirements have been reported in patients receiving nifedipine together with a beta-blocking agent who underwent coronary artery bypass surgery using high dose fentanyl anesthesia. The interaction with high dose fentanyl appears to be due to the combination of nifedipine and a beta blocker, but the possibility that it may occur with nifedipine alone, with low doses of fentanyl, in other surgical procedures, or with other narcotic analgesics cannot be ruled out. In nifedipine treated patients where surgery using high dose fentanyl anesthesia is contemplated, the physician should be aware of these potential problems and, if the patient's condition permits, sufficient time (at least 36 hours) should be allowed for nifedipine to be washed out of the body prior to surgery.

Increased Angina and/or Myocardial Infarction

Rarely, patients, particularly those who have severe obstructive coronary artery disease, have developed well documented increased frequency, duration, and/or severity of angina or acute myocardial infarction on starting nifedipine or at the time of dosage increase. The mechanism of this effect is not established.

Several well-controlled, randomized trials studied the use of immediate-release nifedipine in patients who had just sustained myocardial infarctions. In none of these trials did immediate-release nifedipine appear to provide any benefit. In some of the trials, patients who received immediate-release nifedipine had significantly worse outcomes than patients who received placebo. Nifedipine capsules should not be administered within the first week or two after myocardial infarction, and they should also be avoided in the setting of acute coronary syndrome (when infarction may be imminent).

Use in Essential Hypertension

Nifedipine and other immediate-release nifedipine capsules have also been used for the long-term control of essential hypertension, although nifedipine capsules have not been approved for this purpose and no properly controlled studies have been conducted to define an appropriate dose or dose interval for such treatment. Nifedipine capsules should not be used for the control of essential hypertension.

Beta Blocker Withdrawal

Patients recently withdrawn from beta blockers may develop a withdrawal syndrome with increased angina, probably related to increased sensitivity to catecholamines. Initiation of nifedipine treatment will not prevent this occurrence and might be expected to exacerbate it by provoking reflex catecholamine release. There have been occasional reports of increased angina in a setting of beta blocker withdrawal and nifedipine initiation. It is important to taper beta blockers if possible, rather than stopping them abruptly before beginning nifedipine.

Congestive Heart Failure

Rarely, patients, usually those receiving a beta blocker, have developed heart failure after beginning nifedipine. Patients with tight aortic stenosis may be at greater risk for such an event, as the unloading effect of nifedipine would be expected to be of less benefit to these patients, owing to their fixed impedance to flow across the aortic valve.

PRECAUTIONS

General:

Hypotension:

Because nifedipine decreases peripheral vascular resistance, careful monitoring of blood pressure during the initial administration and titration of nifedipine is suggested. Close observation is especially recommended for patients already taking medications that are known to lower blood pressure. (See WARNINGS.)

Peripheral Edema:

Mild to moderate peripheral edema, typically associated with arterial vasodilation and not due to left ventricular dysfunction, occurs in about one in ten patients treated with nifedipine. This edema occurs primarily in the lower extremities and usually responds to diuretic therapy. With patients whose angina is complicated by congestive heart failure, care should be taken to differentiate this peripheral edema from the effects of increasing left ventricular dysfunction.

Laboratory Tests:

Rare, usually transient, but occasionally significant elevations of enzymes such as alkaline phosphatase, CPK, LDH, SGOT, and SGPT have been noted. The relationship to nifedipine therapy is uncertain in most cases, but probable in some. These laboratory abnormalities have rarely been associated with clinical symptoms; however, cholestasis with or without jaundice has been reported. Rare instances of allergic hepatitis have been reported.

Nifedipine, like other calcium channel blockers, decreases platelet aggregation in vitro. Limited clinical studies have demonstrated a moderate but statistically significant decrease in platelet aggregation and an increase in bleeding time in some nifedipine patients. This is thought to be a function of inhibition of calcium transport across the platelet membrane. No clinical significance for these findings has been demonstrated.

Positive direct Coombs Test with/without hemolytic anemia has been reported but a causal relationship between nifedipine administration and positivity of this laboratory test, including hemolysis, could not be determined.

Although nifedipine has been used safely in patients with renal dysfunction and has been reported to exert a beneficial effect, in certain cases, rare, reversible elevations in BUN and serum creatinine have been reported in patients with pre-existing chronic renal insufficiency. The relationship to nifedipine therapy is uncertain in most cases but probable in some.

Drug Interactions:

Beta-adrenergic blocking agents:

(See INDICATIONS AND USAGE and WARNINGS.) Experience in over 1,400 patients in a non-comparative clinical trial has shown that concomitant administration of nifedipine and beta-blocking agents is usually well tolerated, but there have been occasional literature reports suggesting that the combination may increase the likelihood of congestive heart failure, severe hypotension, or exacerbation of angina.

Long-acting nitrates:

Nifedipine may be safely co-administered with nitrates, but there have been no controlled studies to evaluate the antianginal effectiveness of this combination.

Digitalis:

Since there have been isolated reports of patients with elevated digoxin levels, and since there is a possible interaction between digoxin and nifedipine, it is recommended that digoxin levels be monitored when initiating, adjusting, and discontinuing nifedipine to avoid possible over- or under-digitalization.

Quinidine:

There have been rare reports of an interaction between quinidine and nifedipine (with a decreased plasma level of quinidine).

Coumarin anticoagulants:

There have been rare reports of increased prothrombin time in patients taking coumarin anticoagulants to whom nifedipine was administered. However, the relationship to nifedipine therapy is uncertain.

Cimetidine:

A study in six healthy volunteers has shown a significant increase in peak nifedipine plasma levels (80%) and area-under-the-curve (74%) after a one week course of cimetidine at 1,000 mg per day and nifedipine at 40 mg per day. Ranitidine produced smaller, non-significant increases. The effect may be mediated by the known inhibition of cimetidine on hepatic cytochrome P-450, the enzyme system probably responsible for the first-pass metabolism of nifedipine. If nifedipine therapy is initiated in a patient currently receiving cimetidine, cautious titration is advised.

Nifedipine is metabolized by CYP3A4. Co-administration of nifedipine with phenytoin, an inducer of CYP3A4, lowers the systemic exposure to nifedipine by approximately 70%. Avoid co-administration of nifedipine with phenytoin or any known CYP3A4 inducer or consider an alternative antihypertensive therapy.

CYP3A inhibitors such as fluconazole, itraconazole, clarithromycin, erythromycin, nefazodone, fluoxetine, saquinavir, indinavir, and nelfinavir may result in increased exposure to nifedipine when co-administered. Careful monitoring and dose adjustment may be necessary; consider initiating nifedipine at the lowest dose available if given concomitantly with these medications.

Other Interactions

Grapefruit Juice:

Co-administration of nifedipine with grapefruit juice resulted in approximately a doubling in nifedipine AUC and Cmaxwith no change in half-life. The increased plasma concentrations most likely result from inhibition of CYP3A4 related first-pass metabolism. Avoid ingestion of grapefruit and grapefruit juice while taking nifedipine.

Carcinogenesis, Mutagenesis, Impairment of Fertility:

Nifedipine was administered orally to rats for two years and was not shown to be carcinogenic. When given to rats prior to mating, nifedipine caused reduced fertility at a dose approximately 5 times the maximum recommended human dose. There is a literature report of reversible reduction in the ability of human sperm obtained from a limited number of infertile men taking recommended doses of nifedipine to bind to and fertilize an ovum in vitro. In vivo mutagenicity studies were negative.

Pregnancy:

Pregnancy Category C:

Nifedipine has been shown to produce teratogenic findings in rats and rabbits, including digital anomalies similar to those reported for phenytoin. Digital anomalies have been reported to occur with other members of the dihydropyridine class and are possibly a result of compromised uterine blood flow. Nifedipine administration was associated with a variety of embryotoxic, placentotoxic, and fetotoxic effects, including stunted fetuses (rats, mice, rabbits), rib deformities (mice), cleft palate (mice), small placentas and underdeveloped chorionic villi (monkeys), embryonic and fetal deaths (rats, mice, rabbits), and prolonged pregnancy/decreased neonatal survival (rats; not evaluated in other species). On a mg/kg basis, all of the doses associated with the teratogenic embryotoxic or fetotoxic effects in animals were higher (5 to 50 times) than the maximum recommended human dose of 120 mg/day. On a mg/m^2 basis, some doses were higher and some were lower than the maximum recommended human dose but all were within an order of magnitude of it. The doses associated with placentotoxic effects in monkeys were equivalent to or lower than the maximum recommended human dose on a mg/m^2 basis.

There are no adequate and well-controlled studies in pregnant women. Nifedipine should be used during pregnancy only if the potential benefit justifies the potential risk.

Lactation:

Nifedipine is transferred through breast milk. Nifedipine should be used during breast-feeding only if the potential benefit justifies the potential risk.

Pediatric Use:

Safety and effectiveness in pediatric patients have not been established. Use in pediatric population is not recommended.

Geriatric Use:

Age appears to have a significant effect on the pharmacokinetics of nifedipine. The clearance is decreased resulting in a higher AUC in the elderly. These changes are not due to changes in renal function (see CLINICAL PHARMACOLOGY, Pharmacokinetics).

ADVERSE REACTIONS

In multiple-dose United States and foreign controlled studies in which adverse reactions were reported spontaneously, adverse effects were frequent but generally not serious and rarely required discontinuation of therapy or dosage adjustment. Most were expected consequences of the vasodilator effects of nifedipine.

Adverse Effect | Nifedipine (%) (N=226) | Placebo (%) (N=235)
Dizziness, lightheadedness, giddiness | 27 | 15
Flushing, heat sensation | 25 | 8
Headache | 23 | 20
Weakness | 12 | 10
Nausea, heartburn | 11 | 8
Muscle cramps, tremor | 8 | 3
Peripheral edema | 7 | 1
Nervousness, mood changes | 7 | 4
Palpitation | 7 | 5
Dyspnea, cough, wheezing | 6 | 3
Nasal congestion, sore throat | 6 | 8

There is also a large uncontrolled experience in over 2,100 patients in the United States. Most of the patients had vasospastic or resistant angina pectoris, and about half had concomitant treatment with beta-adrenergic blocking agents. The most common adverse events were:

Incidence Approximately 10%

Cardiovascular: peripheral edema

Central Nervous System: dizziness or lightheadedness

Gastrointestinal: nausea

Systemic: headache and flushing, weakness

Incidence Approximately 5%

Cardiovascular: transient hypotension

Incidence 2% or Less

Cardiovascular: palpitation

Respiratory: nasal and chest congestion, shortness of breath

Gastrointestinal: diarrhea, constipation, cramps, flatulence

Musculoskeletal: inflammation, joint stiffness, muscle cramps

Central Nervous System: shakiness, nervousness, jitteriness, sleep disturbances, blurred vision, difficulties in balance

Other: dermatitis, pruritus, urticaria, fever, sweating, chills, sexual difficulties

Incidence Approximately 0.5%

Cardiovascular: syncope (mostly with initial dosing and/or an increase in dose), erythromelalgia

Incidence Less Than 0.5%

Hematologic: thrombocytopenia, anemia, leukopenia, purpura

Gastrointestinal: allergic hepatitis

Face and Throat: angioedema (mostly oropharyngeal edema with breathing difficulty in a few patients), gingival hyperplasia

CNS: depression, paranoid syndrome

Special Senses: transient blindness at the peak of plasma level, tinnitus

Urogenital: nocturia, polyuria

Other: arthritis with ANA (+), exfoliative dermatitis, gynecomastia

Musculoskeletal: myalgia

Several of these side effects appear to be dose related. Peripheral edema occurred in about one in 25 patients at doses less than 60 mg per day and in about one patient in eight at 120 mg per day or more. Transient hypotension, generally of mild to moderate severity and seldom requiring discontinuation of therapy, occurred in one of 50 patients at less than 60 mg per day and in one of 20 patients at 120 mg per day or more.

Very rarely, introduction of nifedipine therapy was associated with an increase in anginal pain, possibly due to associated hypotension. Transient unilateral loss of vision has also occurred.

In addition, more serious adverse events were observed, not readily distinguishable from the natural history of the disease in these patients. It remains possible, however, that some or many of these events were drug related. Myocardial infarction occurred in about 4% of patients and congestive heart failure or pulmonary edema in about 2%. Ventricular arrhythmias or conduction disturbances each occurred in fewer than 0.5% of patients.

In a subgroup of over 1,000 patients receiving nifedipine with concomitant beta blocker therapy, the pattern and incidence of adverse experiences were not different from that of the entire group of nifedipine treated patients. (See PRECAUTIONS.)

In a subgroup of approximately 250 patients with a diagnosis of congestive heart failure as well as angina pectoris (about 10% of the total patient population), dizziness or lightheadedness, peripheral edema, headache, or flushing each occurred in one in eight patients. Hypotension occurred in about one in 20 patients. Syncope occurred in approximately one patient in 250. Myocardial infarction or symptoms of congestive heart failure each occurred in about one patient in 15. Atrial or ventricular dysrhythmias each occurred in about one patient in 150.

In post-marketing experience, there have been rare reports of exfoliative dermatitis caused by nifedipine. There have been rare reports of exfoliative or bullous skin adverse events (such as erythema multiforme, Stevens-Johnson Syndrome, and toxic epidermal necrolysis) and photosensitivity reactions. Acute generalized exanthematous pustulosis also has been reported.

To report SUSPECTED ADVERSE REACTIONS, contact Chartwell RX, LLC. at 1-845-232-1683 or FDA at 1-800-FDA-1088 or www.fda.gov/medwatch.

OVERDOSAGE

Experience with nifedipine overdosage is limited. Generally, overdosage with nifedipine leading to pronounced hypotension calls for active cardiovascular support including monitoring of cardiovascular and respiratory function, elevation of extremities, and judicious use of calcium infusion, pressor agents, and fluids. Clearance of nifedipine would be expected to be prolonged in patients with impaired liver function. Since nifedipine is highly protein bound, dialysis is not likely to be of any benefit; however, plasmapheresis may be beneficial.

DOSAGE AND ADMINISTRATION

The dosage of nifedipine needed to suppress angina and that can be tolerated by the patient must be established by titration. Excessive doses can result in hypotension.

Therapy should be initiated with the 10 mg capsule. The starting dose is one 10 mg capsule, swallowed whole, 3 times/day. The usual effective dose range is 10 to 20 mg three times daily. Some patients, especially those with evidence of coronary artery spasm, respond only to higher doses, more frequent administration, or both. In such patients, doses of 20 to 30 mg three or four times daily may be effective. Doses above 120 mg daily are rarely necessary. More than 180 mg per day is not recommended.

In most cases, nifedipine titration should proceed over a 7 to 14 day period so that the physician can assess the response to each dose level and monitor the blood pressure before proceeding to higher doses.

If symptoms so warrant, titration may proceed more rapidly provided that the patient is assessed frequently. Based on the patient's physical activity level, attack frequency, and sublingual nitroglycerin consumption, the dose of nifedipine may be increased from 10 mg t.i.d. to 20 mg t.i.d. and then to 30 mg t.i.d. over a three-day period.

In hospitalized patients under close observation, the dose may be increased in 10 mg increments over four- to six-hour periods as required to control pain and arrhythmias due to ischemia. A single dose should rarely exceed 30 mg.

Avoid co-administration of nifedipine with grapefruit juice (see CLINICAL PHARMACOLOGYand PRECAUTIONS: Other Interactions).

No "rebound effect" has been observed upon discontinuation of nifedipine. However, if discontinuation of nifedipine is necessary, sound clinical practice suggests that the dosage should be decreased gradually with close physician supervision.

Co-Administration with Other Antianginal Drugs

Sublingual nitroglycerin may be taken as required for the control of acute manifestations of angina, particularly during nifedipine titration. See PRECAUTIONS, Drug Interactions,for information on co-administration of nifedipine with beta blockers or long-acting nitrates.

HOW SUPPLIED

Nifedipine Capsules, USP are available as white opaque, oblong soft gelatin capsules containing 10 mg of nifedipine. Each capsule is imprinted with " HP 194" in black ink. They are supplied as follows:

Bottles of 90: 10 mg (NDC 62135-739-90)

Nifedipine Capsules, USP are available as peach opaque, oblong soft gelatin capsules containing 20 mg of nifedipine. Each capsule is imprinted with " HP 195" in black ink. They are supplied as follows:

Bottles of 90: 20 mg (NDC 62135-740-90)

The capsules should be protected from light and moisture and stored at Controlled Room Temperature 68° to 77°F (20° to 25°C); excursions permitted to 15° to 30°C (59° to 86°F), in the manufacturer's original container.

Manufactured for:

Chartwell RX, LLC.

Congers, NY 10920

Revised: 08/2023

L71649

PACKAGE LABEL.PRINCIPAL DISPLAY PANEL

NIFEdipine Capsules, USP 10 mg - NDC 62135-739-90 - 90's Bottle Label

NIFEdipine Capsules, USP 20 mg - NDC 62135-740-90 - 90's Bottle Label